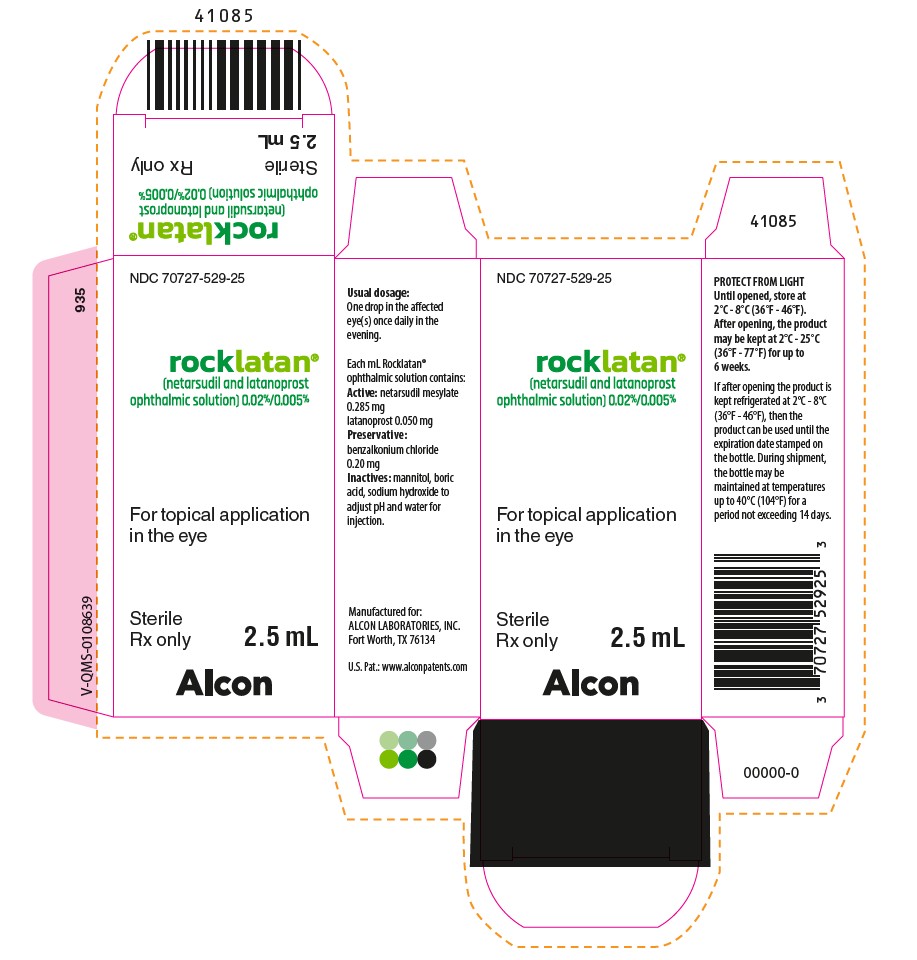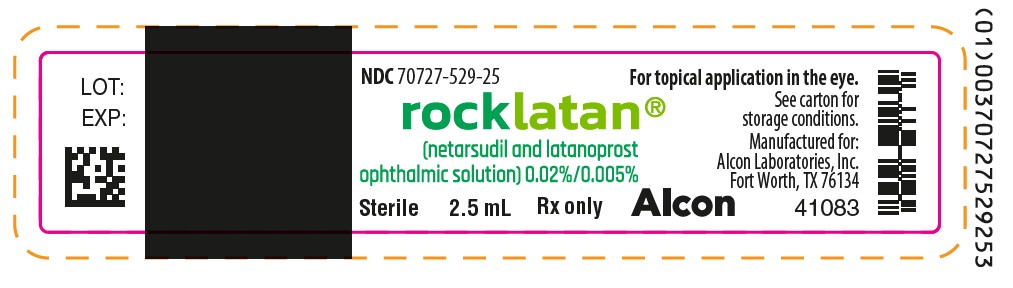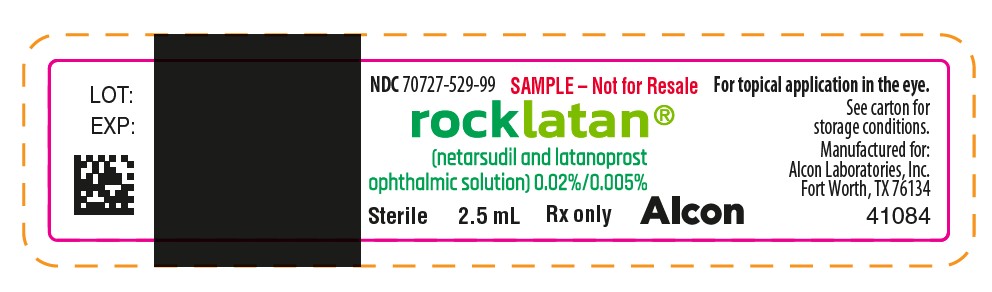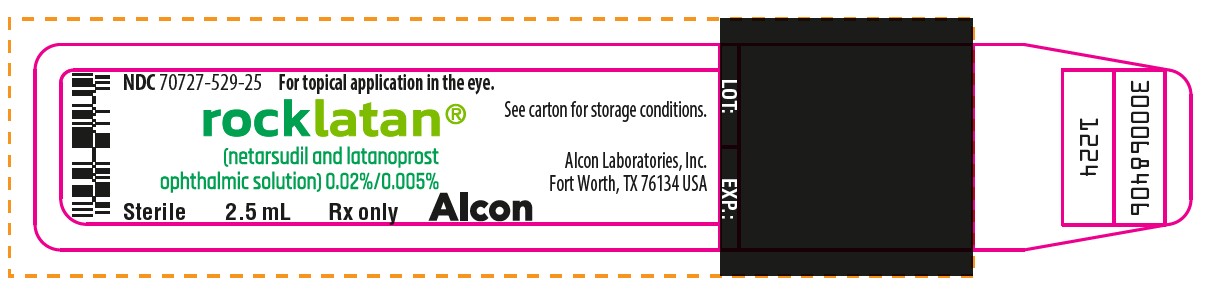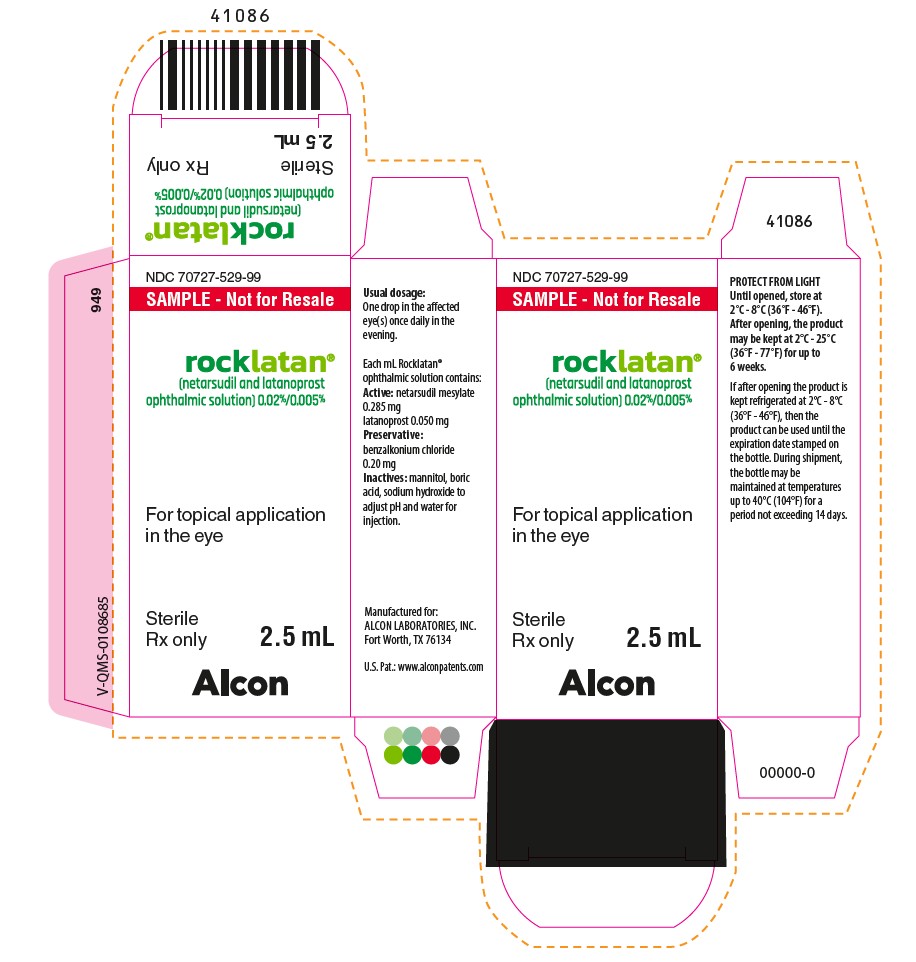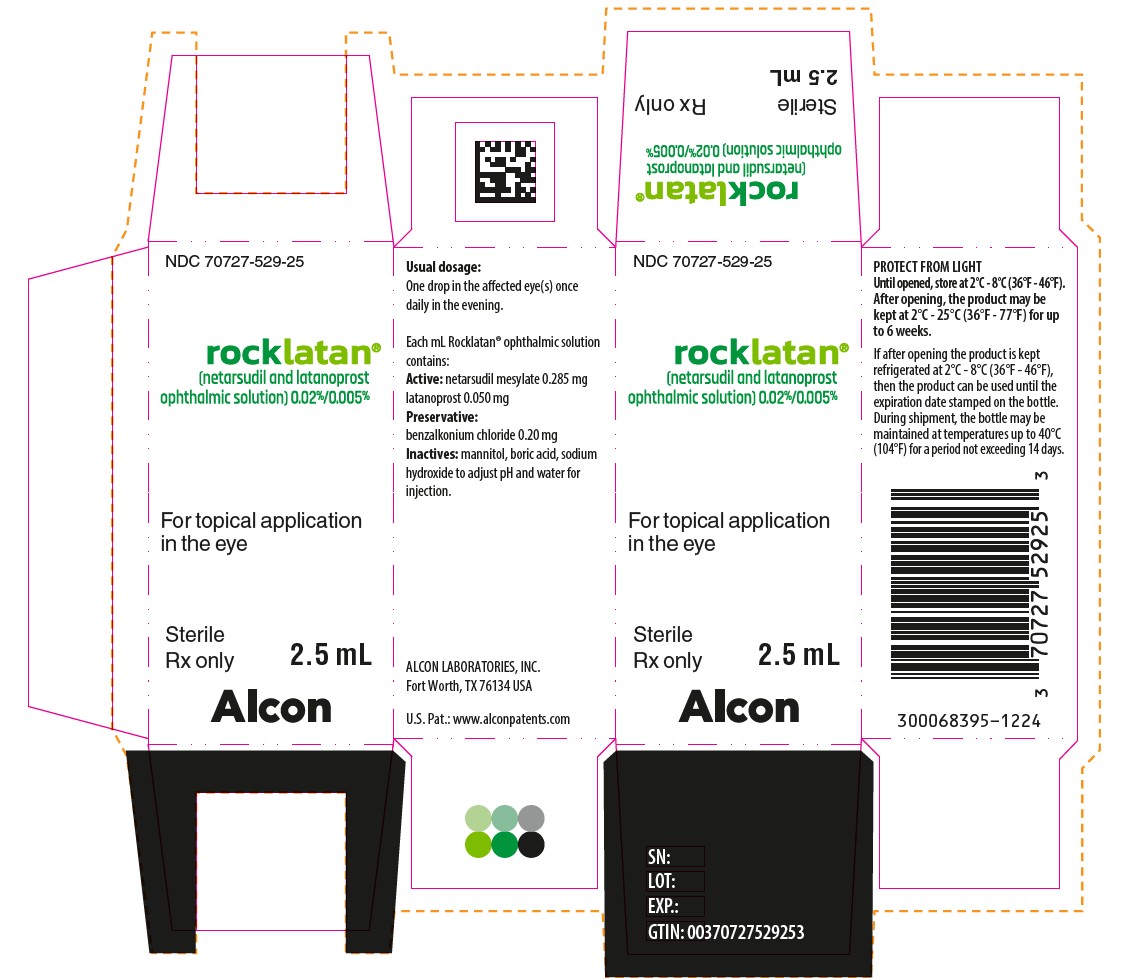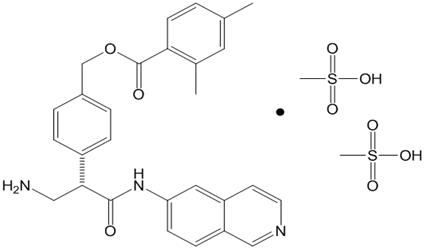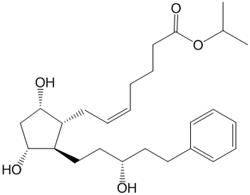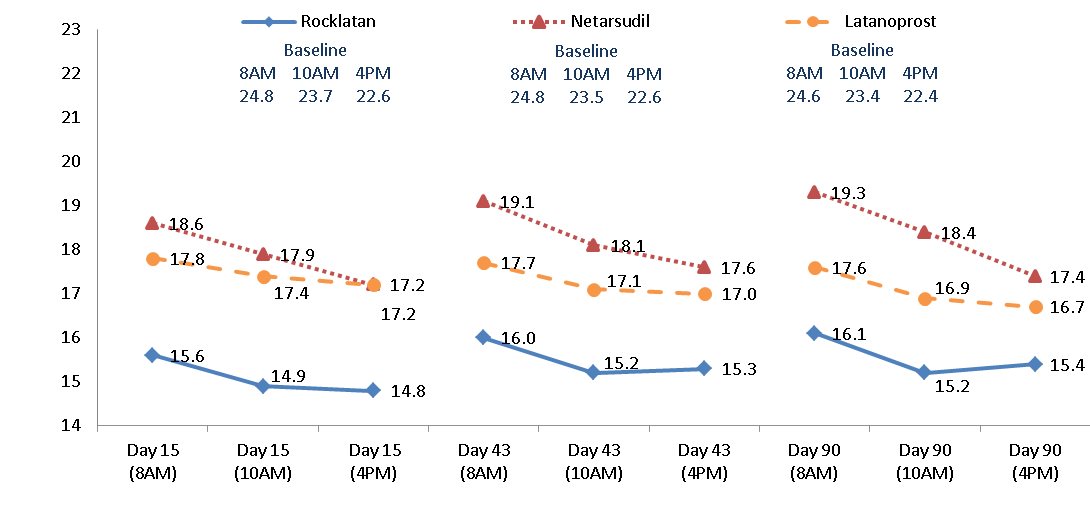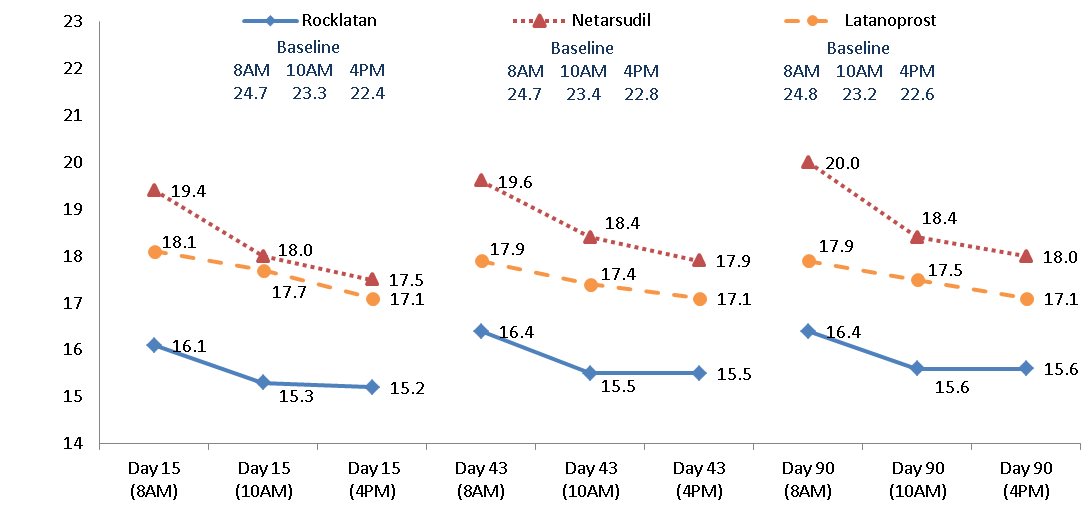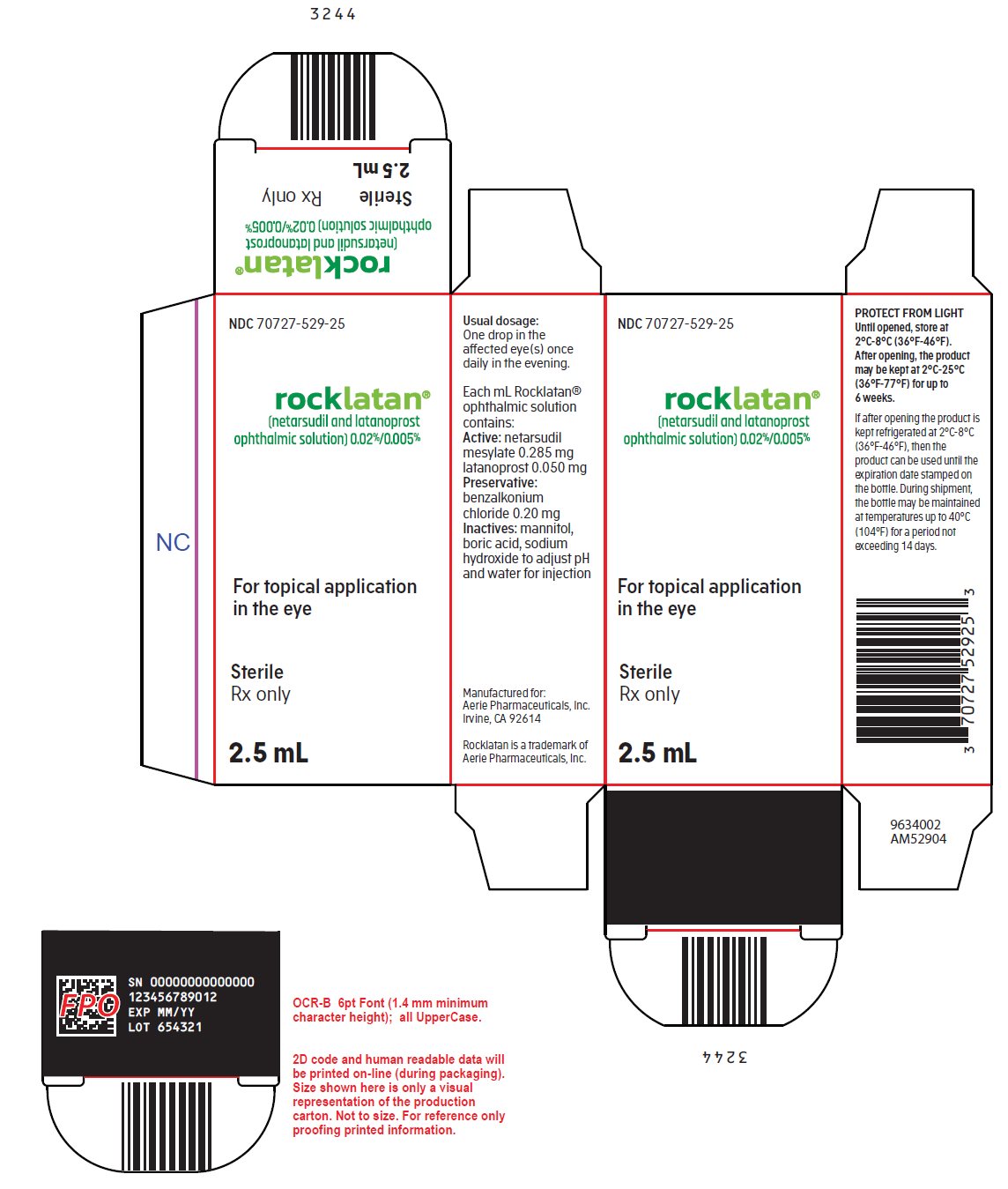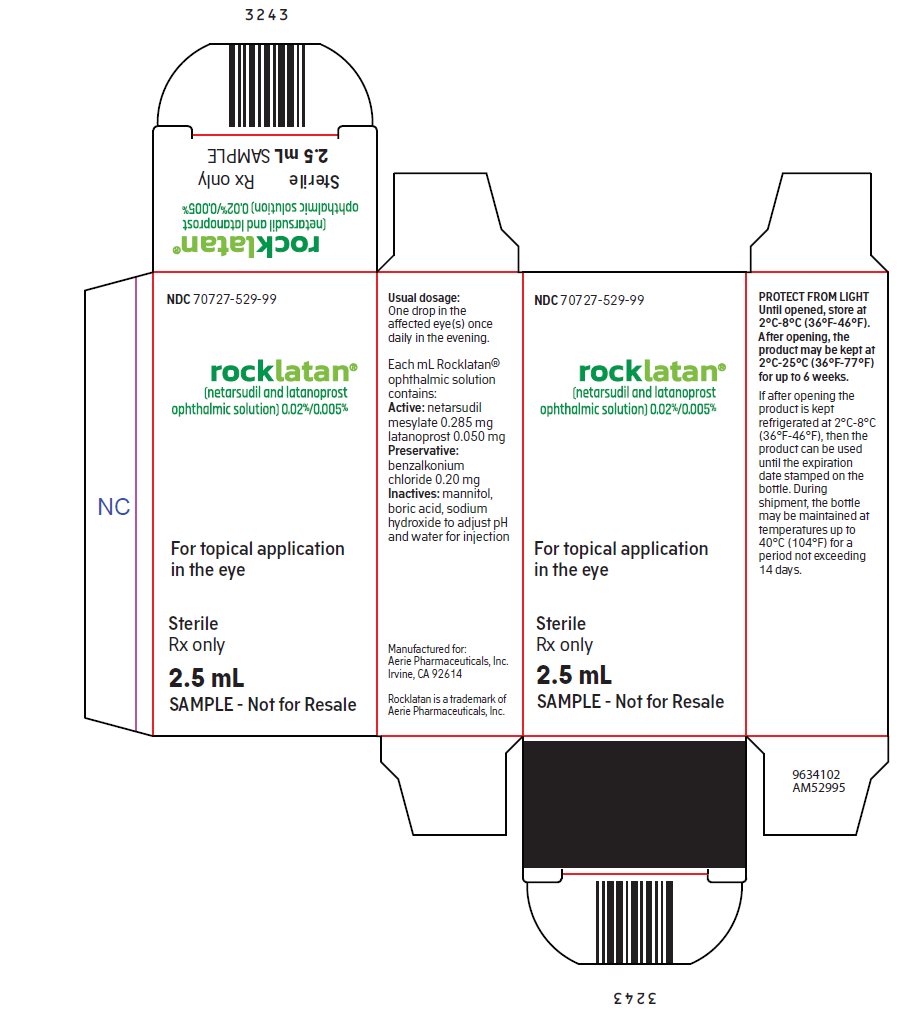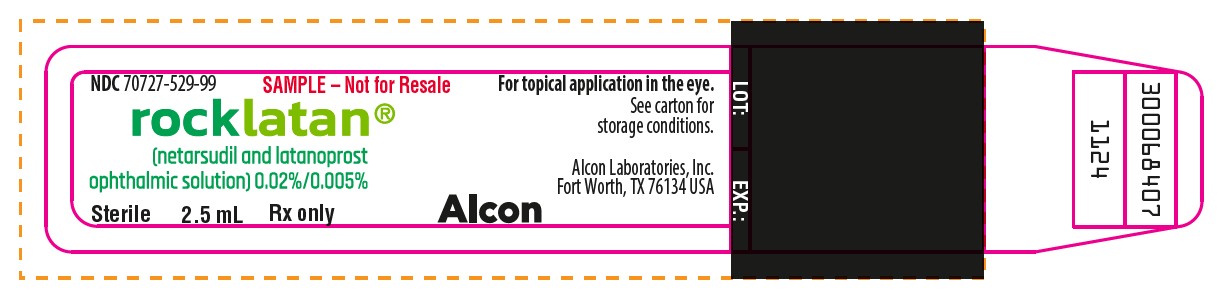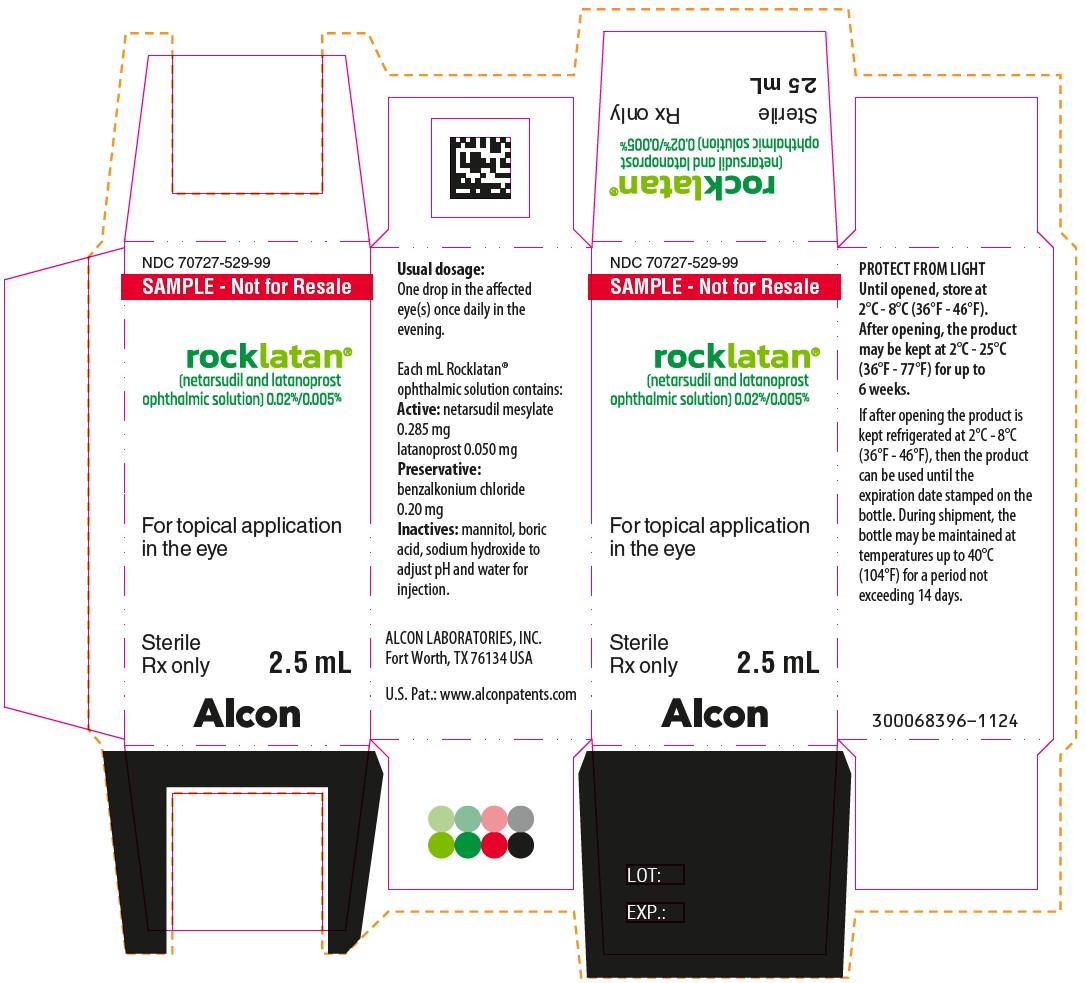 DRUG LABEL: Rocklatan
NDC: 70727-529 | Form: SOLUTION/ DROPS
Manufacturer: Alcon Laboratories, Inc.
Category: prescription | Type: HUMAN PRESCRIPTION DRUG LABEL
Date: 20260120

ACTIVE INGREDIENTS: NETARSUDIL MESYLATE 0.20 mg/1 mL; Latanoprost 0.05 mg/1 mL
INACTIVE INGREDIENTS: BENZALKONIUM CHLORIDE; MANNITOL; BORIC ACID; SODIUM HYDROXIDE; WATER

HIGHLIGHTS OF PRESCRIBING INFORMATION

These highlights do not include all the information needed to use ROCKLATAN® safely and effectively. See full prescribing information for ROCKLATAN®.
ROCKLATAN® (netarsudil and latanoprost ophthalmic solution) 0.02%/0.005%, for topical ophthalmic use
Initial U.S. Approval: 2019

1. INDICATIONS AND USAGE

ROCKLATAN® is a fixed dose combination of a Rho kinase inhibitor and a prostaglandin F2α analogue indicated for the reduction of elevated intraocular pressure (IOP) in patients with open-angle glaucoma or ocular hypertension. (1)

RECENT MAJOR CHANGES

Warnings and Precautions, Epithelial Corneal Edema (5.1) | 01/2025

2. DOSAGE AND ADMINISTRATION

One drop in the affected eye(s) once daily in the evening. (2)

3. DOSAGE FORMS AND STRENGTHS

Ophthalmic solution containing netarsudil 0.02% and latanoprost 0.005%. (3)

4. CONTRAINDICATIONS

None. (4)

5. WARNINGS AND PRECAUTIONS

- Pigmentation: Pigmentation of the iris, periorbital tissue (eyelid) and eyelashes can occur. Iris pigmentation likely to be permanent. (5.2)
- Eyelash Changes: Gradual change to eyelashes including increased length, thickness and number of lashes. Usually reversible. (5.3)

6. ADVERSE REACTIONS

The most common adverse reaction is conjunctival hyperemia (59%). Other common adverse reactions were: instillation site pain (20%), corneal verticillata (15%), and conjunctival hemorrhage (11%). (6.1)
To report SUSPECTED ADVERSE REACTIONS, contact Alcon Laboratories, Inc. at 1 800 757 9195, or FDA at 1-800-FDA-1088 or www.fda.gov/medwatch.

7. DRUG INTERACTIONS

Thimerosal: In vitro studies have shown that precipitation can occur when eye drops containing thimerosal are mixed with ROCKLATAN®. If such drugs are used, they should be administered at least 5 minutes apart. (7)

FULL PRESCRIBING INFORMATION

1. INDICATIONS AND USAGE

ROCKLATAN is a fixed dose combination of a Rho kinase inhibitor and a prostaglandin F2α analogue indicated for the reduction of elevated intraocular pressure (IOP) in patients with open-angle glaucoma or ocular hypertension.

2. DOSAGE AND ADMINISTRATION

The recommended dosage is one drop in the affected eye(s) once daily in the evening. If one dose is missed, treatment should continue with the next dose in the evening. The dosage of ROCKLATAN should not exceed once daily.

ROCKLATAN may be used concomitantly with other topical ophthalmic drug products to lower IOP. If more than one topical ophthalmic drug is being used, the drugs should be administered at least five (5) minutes apart.

3. DOSAGE FORMS AND STRENGTHS

Ophthalmic solution containing netarsudil 0.02% (0.2 mg/mL) and latanoprost 0.005% (0.05 mg/mL).

4. CONTRAINDICATIONS

None.

5. WARNINGS AND PRECAUTIONS

5.1 Epithelial Corneal Edema

ROCKLATAN contains netarsudil which has been associated with Epithelial corneal edema, described as honeycomb or bullous, and has been reported in some patients with pre-existing corneal stromal edema or following ocular procedures that could affect corneal endothelial function. Epithelial corneal edemal typically resolves upon discontinuation of ROCKLATAN. Advise patients to notify their physician if they experience eye pain or decreased vision while using ROCKLATAN [see Adverse Reactions (6.2) and Patient Counselling Information (17)].

5.2 Pigmentation

ROCKLATAN contains latanoprost which has been reported to cause changes to pigmented tissues. The most frequently reported changes have been increased pigmentation of the iris, periorbital tissue (eyelid), and eyelashes. Pigmentation is expected to increase as long as latanoprost is administered.

The pigmentation change is due to increased melanin content in the melanocytes rather than to an increase in the number of melanocytes. After discontinuation of latanoprost, pigmentation of the iris is likely to be permanent, while pigmentation of the periorbital tissue and eyelash changes have been reported to be reversible in some patients. Patients who receive treatment should be informed of the possibility of increased pigmentation. Beyond 5 years the effects of increased pigmentation are not known.

Iris color change may not be noticeable for several months to years. Typically, the brown pigmentation around the pupil spreads concentrically towards the periphery of the iris and the entire iris or parts of the iris become more brownish. Neither nevi nor freckles of the iris appear to be affected by treatment. While treatment with ROCKLATAN can be continued in patients who develop noticeably increased iris pigmentation, these patients should be examined regularly [see Patient Counseling Information (17)].

5.3 Eyelash Changes

ROCKLATAN contains latanoprost which may gradually change eyelashes and vellus hair in the treated eye; these changes include increased length, thickness, pigmentation, the number of lashes or hairs, and misdirected growth of eyelashes. Eyelash changes are usually reversible upon discontinuation of treatment [see Patient Counseling Information (17)].

5.4 Intraocular Inflammation

ROCKLATAN contains latanoprost which should be used with caution in patients with a history of intraocular inflammation (iritis/uveitis) and should generally not be used in patients with active intraocular inflammation because it may exacerbate inflammation.

5.5 Macular Edema

Macular edema, including cystoid macular edema, has been reported during treatment with latanoprost. ROCKLATAN should be used with caution in aphakic patients, in pseudophakic patients with a torn posterior lens capsule, or in patients with known risk factors for macular edema.

5.6 Herpetic Keratitis

Reactivation of Herpes Simplex keratitis has been reported during treatment with latanoprost. ROCKLATAN should be used with caution in patients with a history of herpetic keratitis. ROCKLATAN should be avoided in cases of active herpes simplex keratitis because it may exacerbate inflammation.

5.7 Bacterial Keratitis

There have been reports of bacterial keratitis associated with the use of multiple-dose containers of topical ophthalmic products. These containers had been inadvertently contaminated by patients who, in most cases, had a concurrent corneal disease or a disruption of the ocular epithelial surface [see Patient Counseling Information (17)].

5.8 Use with Contact Lenses

Contact lenses should be removed prior to the administration of ROCKLATAN and may be reinserted 15 minutes after administration.

6. ADVERSE REACTIONS

6.1 Clinical Trials Experience

Because clinical trials are conducted under widely varying conditions, adverse reaction rates observed in the clinical trials of a drug cannot be directly compared to rates in the clinical trials of another drug and may not reflect the rates observed in clinical practice.

The most common ocular adverse reaction observed in controlled clinical studies with ROCKLATAN was conjunctival hyperemia which was reported in 59% of patients. Five percent of patients discontinued therapy due to conjunctival hyperemia. Other common ocular adverse reactions reported were: instillation site pain (20%), corneal verticillata (15%), and conjunctival hemorrhage (11%). Eye pruritus, visual acuity reduced, increased lacrimation, instillation site discomfort, and blurred vision were reported in 5-8% of patients.

Other adverse reactions from clinical trials that have been reported with the individual components and not listed above include:

Netarsudil 0.02%

Instillation site erythema, corneal staining, increased lacrimation, and erythema of eyelid.

Latanoprost 0.005%

Foreign body sensation, punctate keratitis, burning and stinging, itching, increased pigmentation of the iris, excessive tearing, eyelid discomfort, dry eye, eye pain, eyelid margin crusting, erythema of the eyelid, upper respiratory tract infection/nasopharyngitis/influenza, photophobia, eyelid edema, myalgia/arthralgia/back pain, and rash/allergic reactions.

6.2 Postmarketing Experience

The following adverse reactions have been identified during postmarketing use of ROCKLATAN. Because these reactions are reported voluntarily from a population of uncertain size, it is not always possible to reliably estimate their frequency or establish a causal relationship to drug exposure.

Netarsudil 0.02%

Eye disorders: Epithelial corneal edema has been reported in some patients with pre-existing corneal stromal edema or ocular procedures that could affect corneal endothelial function. [see Warnings and Precautions (5.1)].

7. DRUG INTERACTIONS

In vitro drug interaction studies have shown that precipitation can occur when eye drops containing thimerosal are mixed with ROCKLATAN. If such drugs are used, they should be administered at least five (5) minutes apart.

The combined use of two or more prostaglandins or prostaglandin analogs including latanoprost ophthalmic solution 0.005% is not recommended. It has been shown that administration of these prostaglandin drug products more than once daily may decrease the IOP lowering effect or cause paradoxical elevations in IOP.

8. USE IN SPECIFIC POPULATIONS

8.1 Pregnancy

Risk Summary
There are no adequate and well-controlled studies of ROCKLATAN ophthalmic solution or its pharmacologically active ingredients (netarsudil and latanoprost) in pregnant women to inform any drug associated risk. However, systemic exposure to netarsudil from ocular administration is low [see Clinical Pharmacology (12.3)].

Reproduction studies of latanoprost showed embryofetal lethality in rabbits. No embryofetal lethality was observed at a dose approximately 15 times higher than the recommended human ophthalmic dose (RHOD). Intravenous administration of netarsudil to pregnant rats and rabbits during organogenesis did not produce adverse embryofetal effects at clinically relevant systemic exposures. ROCKLATAN should be used during pregnancy only if the potential benefit justifies the potential risk to the fetus.

Data
Animal Data
Netarsudil administered daily by intravenous injection to rats during organogenesis caused abortions and embryofetal lethality at doses ≥0.3 mg/kg/day (126-fold the plasma exposure at the RHOD, based on Cmax). The no-observed-adverse-effect-level (NOAEL) for embryofetal development toxicity was 0.1 mg/kg/day (40-fold the plasma exposure at the RHOD, based on Cmax).

Netarsudil administered daily by intravenous injection to rabbits during organogenesis caused embryofetal lethality and decreased fetal weight at 5 mg/kg/day (1480-fold the plasma exposure at the RHOD, based on Cmax). Malformations were observed at ≥3 mg/kg/day (1330-fold the plasma exposure at the RHOD, based on Cmax), including thoracogastroschisis, umbilical hernia and absent intermediate lung lobe. The NOAEL for embryofetal development toxicity was 0.5 mg/kg/day (214-fold the plasma exposure at the RHOD, based on Cmax).

Reproduction studies have been performed with latanoprost in rats and rabbits. In 4 of 16 pregnant rabbits, no viable fetuses were present at a dose that was approximately 80 times higher than the RHOD. Latanoprost did not produce embryofetal lethality in rabbits at a dose approximately 15 times higher than the RHOD.

8.2 Lactation

Risk Summary
There are no data on the presence of netarsudil or latanoprost in human milk, the effects on the breastfed infant, or the effects on milk production. However, systemic exposure to netarsudil following topical ocular administration is low, and it is not known whether measurable levels of netarsudil would be present in maternal milk following topical ocular administration.

The developmental and health benefits of breastfeeding should be considered along with the mother’s clinical need for ROCKLATAN and any potential adverse effects on the breast-fed child from ROCKLATAN.

8.4 Pediatric Use

Safety and effectiveness in pediatric patients have not been established.

8.5 Geriatric Use

No overall differences in safety or effectiveness have been observed between elderly and other adult patients.

11. DESCRIPTION

ROCKLATAN (netarsudil and latanoprost ophthalmic solution) 0.02%/0.005% is a fixed dose combination of a Rho kinase inhibitor and a prostaglandin F2α analogue.

The chemical name of netarsudil dimesylate is: (S)-4-(3-amino-1-(isoquinolin-6-yl-amino)-1-oxopropan-2-yl)benzyl 2,4-dimethylbenzoate dimesylate. Its molecular formula is C30H35N3O9S2 and its chemical structure is:

Netarsudil mesylate is a light yellow to white powder that is freely soluble in water, soluble in methanol, sparingly soluble in dimethyl formamide, and practically insoluble in dichloromethane and heptane.

The chemical name of latanoprost is: isopropyl-(Z)-7[1R,2R,3R,5S) 3,5-dihydroxy-2-[(3R)-3-hydroxy-5-phenylpentyl]cyclopentyl]-5-heptenoate. Its molecular formula is C26H40O5 and its chemical structure is:

Latanoprost is a colorless to slightly yellow oil that is very soluble in acetonitrile and freely soluble in acetone, ethanol, ethyl acetate, isopropanol, methanol, and octanol. It is practically insoluble in water.

ROCKLATAN (netarsudil and latanoprost ophthalmic solution) 0.02%/0.005% is supplied as a sterile, isotonic, buffered aqueous solution of netarsudil mesylate and latanoprost with a pH of approximately 5 and an osmolality of approximately 295 mOsmol/kg. Each mL of ROCKLATAN contains 0.20 mg of netarsudil (equivalent to 0.28 mg of netarsudil dimesylate) and 0.05 mg latanoprost. Benzalkonium chloride, 0.02%, is added as a preservative. The inactive ingredients are: boric acid, mannitol, sodium hydroxide to adjust pH, and water for injection.

12. CLINICAL PHARMACOLOGY

12.1 Mechanism of Action

ROCKLATAN is comprised of two components: netarsudil and latanoprost. Each of these two components decreases elevated IOP. Elevated IOP represents a major risk factor for glaucomatous field loss. The higher the level of IOP, the greater the likelihood of optic nerve damage and glaucomatous visual field loss.

ROCKLATAN is believed to reduce IOP by increasing the outflow of aqueous humor.

12.3 Pharmacokinetics

Absorption
The systemic exposures of netarsudil and its active metabolite, AR-13503, were evaluated in 18 healthy subjects after topical ocular administration of netarsudil ophthalmic solution 0.02% once daily (1 drop bilaterally in the morning) for 8 days. There were no quantifiable plasma concentrations of netarsudil (lower limit of quantitation (LLOQ) 0.100 ng/mL) post dose on Day 1 and Day 8. Only 1 plasma concentration at 0.11 ng/mL for the active metabolite was observed for 1 subject on Day 8 at 8 hours post-dose.

Distribution
The distribution volume in humans is 0.16 ± 0.02 L/kg. Latanoprost is absorbed through the cornea where the isopropyl ester prodrug is hydrolyzed to the acid form to become biologically active. The acid of latanoprost can be measured in aqueous humor during the first 4 hours, and in plasma only during the first hour after local administration.

Metabolism
After topical ocular dosing, netarsudil is metabolized by esterases in the eye to an active metabolite, AR-13503.

Latanoprost, an isopropyl ester prodrug, is hydrolyzed by esterases in the cornea to the biologically active acid. The active acid of latanoprost reaching the systemic circulation is primarily metabolized by the liver to the 1,2-dinor and 1,2,3,4-tetranor metabolites via fatty acid β-oxidation.

Excretion
The elimination of the acid of latanoprost from human plasma is rapid (t½ = 17 min) after both intravenous and topical administration. Systemic clearance is approximately 7 mL/min/kg. Following hepatic β-oxidation, the metabolites are mainly eliminated via the kidneys. Approximately 88% and 98% of the administered dose are recovered in the urine after topical and intravenous dosing, respectively.

13. NONCLINICAL TOXICOLOGY

13.1 Carcinogenesis, Mutagenesis, Impairment of Fertility

Carcinogenesis
Long-term studies in animals have not been performed to evaluate the carcinogenic potential of netarsudil.

Latanoprost was not carcinogenic in either mice or rats when administered by oral gavage at doses of up to 170 mcg/kg/day (approximately 2800 times the RHOD) for up to 20 and 24 months, respectively.

Mutagenesis
Netarsudil was not mutagenic in the Ames test, in the mouse lymphoma test, or in the in vivo rat micronucleus test.

Latanoprost was not mutagenic in bacteria, in mouse lymphoma, or in mouse micronucleus tests. Chromosome aberrations were observed in vitro with human lymphocytes. Additional in vitro and in vivo studies on unscheduled DNA synthesis in rats were negative.

Impairment of Fertility
Studies to evaluate the effects of netarsudil on male or female fertility in animals have not been performed.

Latanoprost has not been found to have effects on male or female fertility in animal studies.

14. CLINICAL STUDIES

ROCKLATAN (netarsudil and latanoprost ophthalmic solution) 0.02%/0.005% was evaluated in 2 randomized and controlled clinical trials, namely PG324-CS301 (NCT 02558400, referred to as Study 301) and PG324-CS302 (NCT 02674854, referred to as Study 302) in patients with open-angle glaucoma and ocular hypertension. Studies 301 and 302 enrolled subjects with IOP < 36 mmHg and compared IOP lowering effect of ROCKLATAN dosed once daily to individually administered netarsudil 0.02% once daily and latanoprost 0.005% once daily. The treatment duration was 12 months for Study 301 and 3 months for Study 302.

The average IOP lowering effect of ROCKLATAN was 1 to 3 mmHg greater than monotherapy with either netarsudil 0.02% or latanoprost 0.005% throughout 3 months (Figures 1 and 2). In Study 301 IOP reductions were maintained throughout 12 months.

Figure 1: Study 301 Mean IOP (mmHg) by Treatment Group and Treatment Difference in Mean IOP

Rocklatan vs.; Netarsudil; 95% CI | 3.0 (2.5, 3.6) | 3.0 (2.4, 3.6) | 2.4 (1.9, 3.0) | 3.2 (2.6, 3.8) | 2.9 (2.3, 3.5) | 2.3 (1.7, 2.8) | 3.1 (2.5, 3.8) | 3.2 (2.5, 3.8) | 2.0 (1.4, 2.6)
Rocklatan vs.; Latanoprost; 95% CI | 2.3 (1.7, 2.8) | 2.6 (2.0, 3.2) | 2.3 (1.8, 2.9) | 1.7 (1.1, 2.4) | 1.9 (1.3, 2.5) | 1.7 (1.1, 2.2) | 1.5 (0.9, 2.1) | 1.7 (1.1, 2.3) | 1.3 (0.7, 1.9)

The least square mean IOP at each post-baseline time point was derived using an analysis of covariance adjusted for baseline IOP and based on observed data for all randomized subjects (238 in Rocklatan group, 244 in netarsudil group, 236 in latanoprost group).

Figure 2: Study 302 Mean IOP (mmHg) by Treatment Group and Treatment Difference in Mean IOP

Rocklatan vs.; Netarsudil; 95% CI | 3.4 (2.8, 3.9) | 2.7 (2.2, 3.2) | 2.2 (1.7, 2.8) | 3.2 (2.6, 3.8) | 2.9 (2.3, 3.4) | 2.3 (1.8, 2.9) | 3.6 (3.0, 4.2) | 2.8 (2.3, 3.4) | 2.4 (1.9, 2.9)
Rocklatan vs.; Latanoprost; 95% CI | 2.0 (1.5, 2.6) | 2.4 (1.9, 2.9) | 1.9 (1.3, 2.4) | 1.5 (0.9, 2.1) | 1.9 (1.3, 2.4) | 1.6 (1.0, 2.1) | 1.5 (0.9, 2.2) | 2.0 (1.4, 2.5) | 1.5 (1.0, 2.1)

The least square mean IOP at each post-baseline time point was derived using an analysis of covariance adjusted for baseline IOP and based on observed data for all randomized subjects (245 in Rocklatan group, 255 in netarsudil group, 250 in latanoprost group).

16. HOW SUPPLIED/STORAGE AND HANDLING

ROCKLATAN (netarsudil and latanoprost ophthalmic solution) 0.02%/0.005% is supplied sterile in clear low density polyethylene bottles with opaque white polyethylene dropper tips and white polypropylene screw caps.

2.5 mL fill in a 4 mL container - NDC # 70727-529-25

Storage: Protect from light. Until opened, store at 2°C to 8°C (36°F to 46°F). After opening, the product may be kept at 2°C to 25°C (36°F to 77°F) for up to 6 weeks. If after opening the product is kept refrigerated at 2°C to 8°C (36°F to 46°F), then the product can be used until the expiration date stamped on the bottle. During shipment, the bottle may be maintained at temperatures up to 40°C (104°F) for a period not exceeding 14 days.

17. PATIENT COUNSELING INFORMATION

Potential for Pigmentation
Advise patients about the potential for increased brown pigmentation of the iris, which may be permanent. Inform patients about the possibility of eyelid skin darkening, which may be reversible after discontinuation of ROCKLATAN [see Warnings and Precautions (5.2)].

Potential for Eyelash Changes
Inform patients of the possibility of eyelash and vellus hair changes in the treated eye during treatment with ROCKLATAN. These changes may result in a disparity between eyes in length, thickness, pigmentation, number of eyelashes or vellus hairs, and/or direction of eyelash growth. Eyelash changes are usually reversible upon discontinuation of treatment.

Handling the Container
Instruct patients to avoid allowing the tip of the dispensing container to contact the eye, surrounding structures, fingers, or any other surface in order to minimize contamination of the solution. Serious damage to the eye and subsequent loss of vision may result from using contaminated solutions [see Warnings and Precautions (5.7)].

When to Seek Physician Advice
Advise patients that if they develop an intercurrent ocular condition (e.g., trauma, or infection, or decreased vision with or without eye pain), have ocular surgery, or develop any ocular reactions, particularly conjunctivitis and eyelid reactions, they should immediately seek their physician’s advice concerning the continued use of ROCKLATAN.

Use with Contact Lenses
Advise patients that ROCKLATAN contains benzalkonium chloride, which may be absorbed by soft contact lenses. Contact lenses should be removed prior to instillation of ROCKLATAN and may be reinserted 15 minutes following its administration.

Use with Other Ophthalmic Drugs
If more than 1 topical ophthalmic drug is being used, the drugs should be administered at least 5 minutes between applications.

Missed Dose
Advise patients that if one dose is missed, treatment should continue with the next dose in the evening.

© 2024-2025 Alcon Inc.
U.S. Pat.: www.alconpatents.com
ALCON LABORATORIES, Inc., Fort Worth, Texas 76134
1-800-757-9195
Alcon.medinfo@alcon.com

PACKAGE/LABEL PRINCIPAL DISPLAY PANEL

NDC 70727-529-25
rocklatan®
(netarsudil and latanoprost
ophthalmic solution) 0.02%/0.005%
For topical application
in the eye
Sterile
Rx only
2.5 mL
Usual dosage:
One drop in the affected
eye(s) once daily in the
evening.
Each ml Rocklatan®
ophthalmic solution contains:
Active: netrasudil mesylate
0.285 mg
latanoprost 0.050 mg
Preservative:
benzalkonium chloride
0.20 mg
Inactives: mannitol, boric
acid, sodium hydroxide to
adjust pH and water
for injection.
Manufactured for:
ALCON LABORATORIES, INC.
Fort Worth, TX 76134
U.S. Pat.: www.alconpatents.com
PROTECT FROM LIGHT
Until opened, store at
2°C - 8°C (36°F - 46°F).
After opening, the product
may be kept at 2°C - 25°C
(36°F - 77°F) for up to
6 weeks.
If after opening the product is
kept refrigerated at 2°C - 8°C
(36°F - 46°F), then the
product can be used until the
expiration date stamped on
the bottle During shipment,
the bottle may be
maintained at temperatures
up to 40°C (104°F) for a
period not exceeding 14 days.

NDC 70727-529-25
rocklatan®
(netarsudil and latanoprost
ophthalmic solution) 0.02%/0.005%
Sterile 2.5 mL Rx only
For topical application in the eye.
See carton
for storage conditions.
Manufactured for:
Alcon Laboratories, Inc.
Fort Worth, TX 76134

NDC 70727-529-99
SAMPLE – Not for Resale
rocklatan®
(netarsudil and latanoprost
ophthalmic solution) 0.02%/0.005%
For topical application
in the eye
Sterile
Rx only
2.5 mL
Usual dosage:
One drop in the affected
eye(s) once daily in the
evening.
Each ml Rocklatan®
ophthalmic solution contains:
Active: netrasudil mesylate
0.285 mg
latanoprost 0.050 mg
Preservative:
benzalkonium chloride
0.20 mg
Inactives: mannitol, boric
acid, sodium hydroxide to
adjust pH and water for
injection.
Manufactured for:
ALCON LABORATORIES, INC.
Fort Worth, TX 76134
U.S. Pat.: www.alconpatents.com
PROTECT FROM LIGHT
Until opened, store at
2°C - 8°C (36°F - 46°F).
After opening, the product
may be kept at 2°C - 25°C
(36°F - 77°F) for up to
6 weeks.
If after opening the product is
kept refrigerated at 2°C - 8°C
(36°F - 46°F), then the
product can be used until the
expiration date stamped on
the bottle During shipment,
the bottle may be
maintained at temperatures
up to 40°C (104°F) for a
period not exceeding 14 days.

NDC 70727-529-99 SAMPLE – Not for Resale
rocklatan®
(netarsudil and latanoprost
ophthalmic solution) 0.02%/0.005%
Sterile 2.5 mL Rx only
For topical application in the eye.
See carton for
storage conditions.
Manufactured for:
Alcon Laboratories, Inc.
Fort Worth, TX 76134

NDC 70727-529-25
rocklatan®
(netarsudil and latanoprost
ophthalmic solution) 0.02%/0.005%
For topical application
in the eye
Sterile
Rx only
2.5 mL

NDC 70727-529-99
rocklatan®
(netarsudil and latanoprost
ophthalmic solution) 0.02%/0.005%
For topical application
in the eye
Sterile
Rx only
2.5 mL
SAMPLE – Not for Resale

NDC 70727-529-25
rocklatan®
(netarsudil and latanoprost
ophthalmic solution) 0.02%/0.005%
For topical application
in the eye
Sterile
Rx only
2.5 mL
Alcon
Usual dosage:
One drop in the affected eye(s) once
daily in the evening.
Each ml Rocklatan® ophthalmic solution
contains:
Active: netrasudil mesylate 0.285 mg
latanoprost 0.050 mg
Preservative:
benzalkonium chloride 0.20 mg
Inactives: mannitol, boric acid, sodium
hydroxide to adjust pH and water for
injection.
ALCON LABORATORIES, INC.
Fort Worth, TX 76134 USA
U.S. Pat.: www.alconpatents.com
PROTECT FROM LIGHT
Until opened, store at 2°C - 8°C (36°F - 46°F).
After opening, the product may be
kept at 2°C - 25°C (36°F - 77°F) for up
to 6 weeks.
If after opening the product is kept
refrigerated at 2°C - 8°C (36°F - 46°F),
then the product can be used until the
expiration date stamped on the bottle.
During shipment, the bottle may be
maintained at temperatures up to 40°C
(104°F) for a period not exceeding 14 days.
300068395-1224
SN:
LOT:
EXP.
GTIN: 00370727529253

PACKAGE/LABEL PRINCIPAL DISPLAY PANEL

NDC 70727-529-25 For topical application in the eye.
rocklatan®
(netarsudil and latanoprost
ophthalmic solution) 0.02%/0.005%
Sterile 2.5 mL Rx only Alcon
See carton for storage conditions.
Alcon Laboratories, Inc.
Fort Worth, TX 76134 USA
300068406
1224

PACKAGE/LABEL PRINCIPAL DISPLAY PANEL

NDC 70727-529-99
SAMPLE – Not for Resale
rocklatan®
(netarsudil and latanoprost
ophthalmic solution) 0.02%/0.005%
For topical application
in the eye
Sterile
Rx only 2.5 mL
Usual dosage:
One drop in the affected
eye(s) once daily in the
evening.
Each ml Rocklatan®
ophthalmic solution contains:
Active: netrasudil mesylate
0.285 mg
latanoprost 0.050 mg
Preservative:
benzalkonium chloride
0.20 mg
Inactives: mannitol, boric
acid, sodium hydroxide to
adjust pH and water for
injection.
ALCON LABORATORIES, INC.
Fort Worth, TX 76134 USA
U.S. Pat.: www.alconpatents.com
PROTECT FROM LIGHT
Until opened, store at
2°C - 8°C (36°F - 46°F).
After opening, the product
may be kept at 2°C - 25°C
(36°F - 77°F) for up to
6 weeks.
If after opening the product is
kept refrigerated at 2°C - 8°C
(36°F - 46°F), then the product
can be used until the
expiration date stamped on the
bottle. During shipment, the
bottle may be maintained at
temperatures up to 40°C
(104°F) for a period not
exceeding 14 days.
300068396-1124

PACKAGE/LABEL PRINCIPAL DISPLAY

NDC 70727-529-99 SAMPLE – Not for Resale
rocklatan®
(netarsudil and latanoprost
ophthalmic solution) 0.02%/0.005%
Sterile 2.5 mL Rx only Alcon
For topical application in the eye.
See carton for
storage conditions.
Alcon Laboratories, Inc.
Fort Worth, TX 76134 USA
LOT: EXP.:
300068407
1124